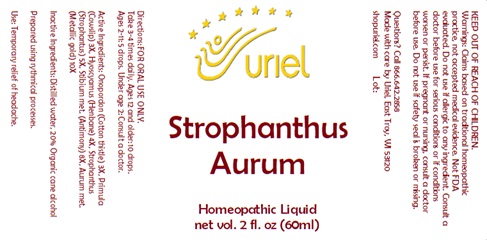 DRUG LABEL: Strophanthus Aurum
NDC: 48951-8403 | Form: LIQUID
Manufacturer: Uriel Pharmacy Inc.
Category: homeopathic | Type: HUMAN OTC DRUG LABEL
Date: 20241219

ACTIVE INGREDIENTS: ONOPORDUM ACANTHIUM FLOWER 3 [hp_X]/1 mL; PRIMULA VERIS FLOWER 3 [hp_X]/1 mL; HYOSCYAMUS NIGER LEAF 4 [hp_X]/1 mL; STROPHANTHUS KOMBE WHOLE 5 [hp_X]/1 mL; ANTIMONY 8 [hp_X]/1 mL; GOLD 10 [hp_X]/1 mL
INACTIVE INGREDIENTS: WATER; ALCOHOL

Strophanthus Aurum

INDICATIONS AND USAGE

Directions: FOR ORAL USE ONLY.

DOSAGE AND ADMINISTRATION

Take 3-4 times daily. Ages 12 and older: 10 drops. Ages 2-11: 5 drops. Under age 2: Consult a doctor.

ACTIVE INGREDIENT

Active Ingredients: Onopordon (Cotton thistle) 3X, Primula (Cowslip) 3X, Hyoscyamus (Henbane) 4X, Strophanthus (Strophantus) 5X, Stibium met. (Antimony) 8X, Aurum met. (Metallic gold) 10X

Inactive Ingredients: Distilled water, 20% Organic cane alcohol

Prepared using rhythmical processes.

PURPOSE

Use: Temporary relief of headache.

KEEP OUT OF REACH OF CHILDREN.

WARNINGS

Warnings: Claims based on traditional homeopathic practice, not accepted medical evidence. Not FDA evaluated. Do not use if allergic to any ingredient. Consult a doctor before use for serious conditions or if conditions worsen or persist. If pregnant or nursing, consult a doctor before use. Do not use if safety seal is broken or missing.

QUESTIONS

Questions? Call 866.642.2858 Made with care by Uriel, East Troy, WI 53120 shopuriel.com Lot: